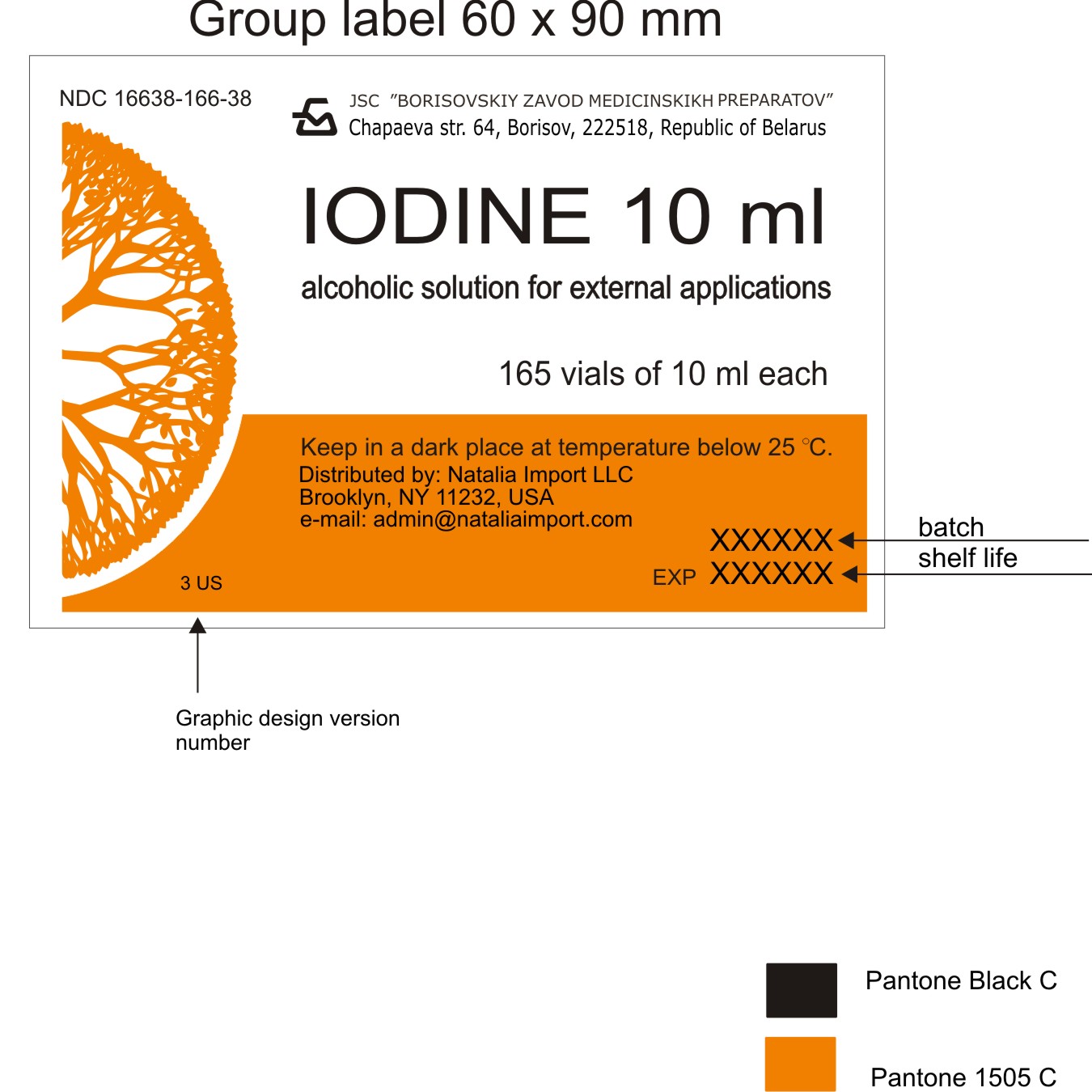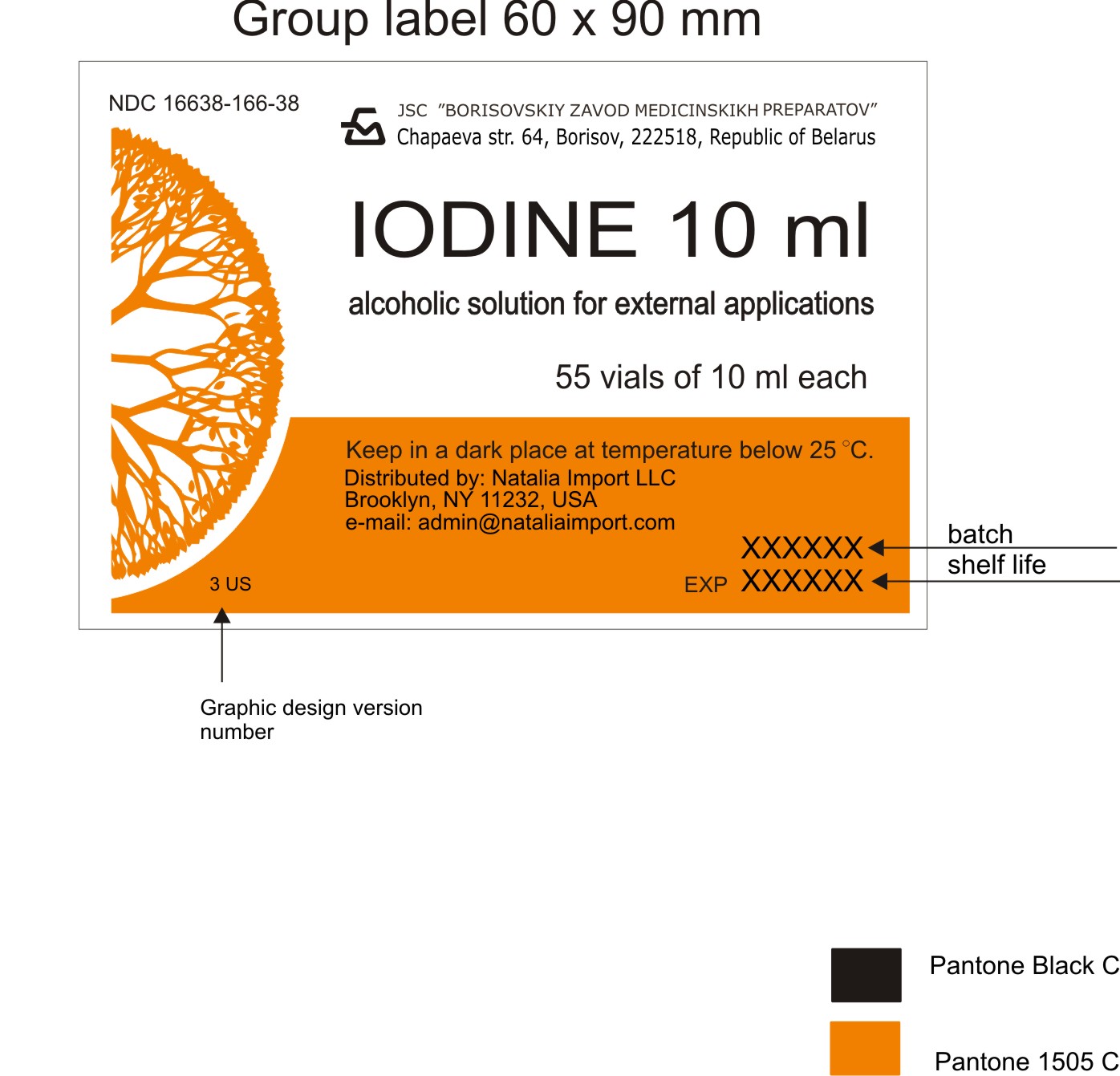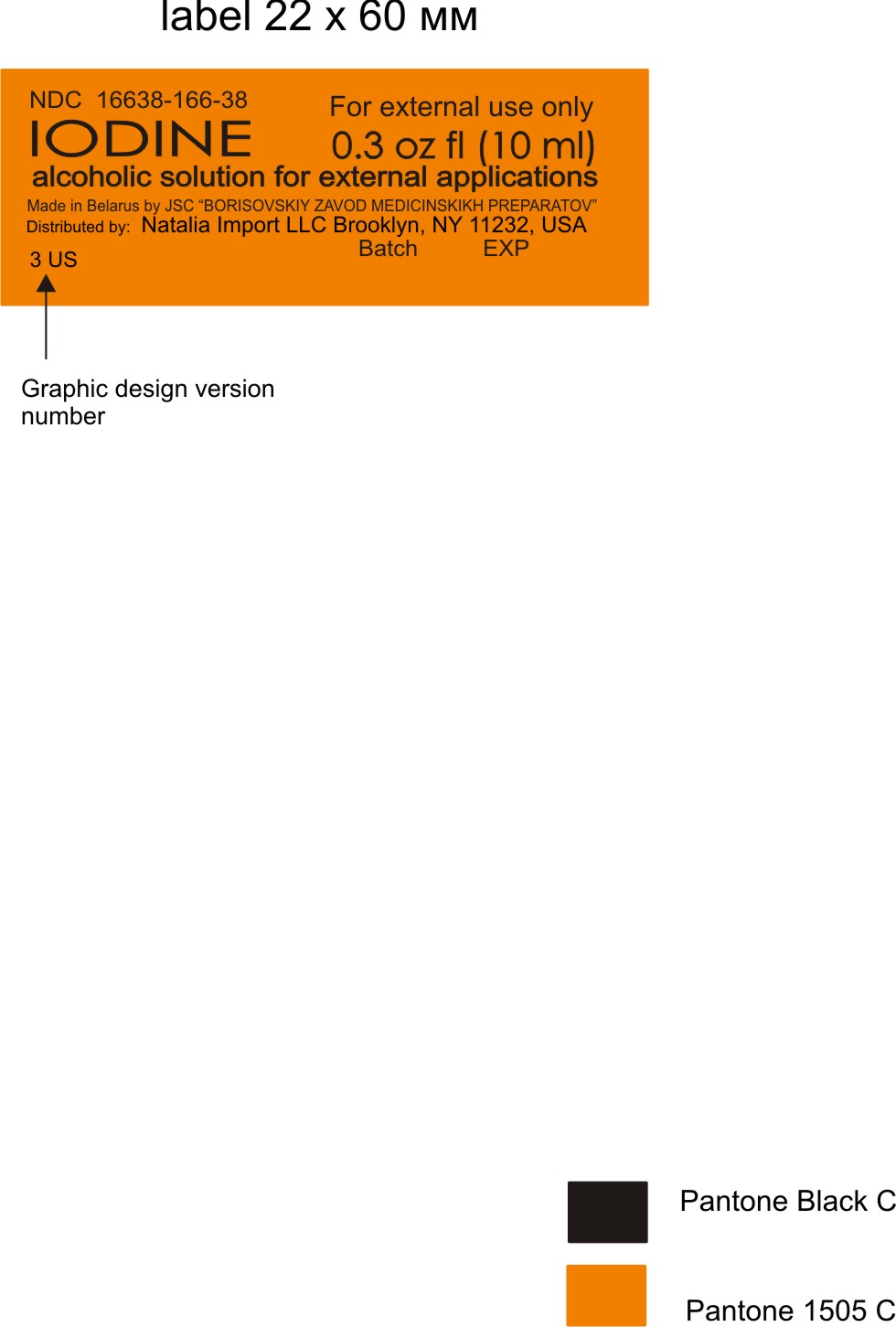 DRUG LABEL: IODINE
NDC: 16638-166 | Form: SOLUTION
Manufacturer: Borisovskiy Zavod Medicinskikh Preparatov JSC
Category: otc | Type: HUMAN OTC DRUG LABEL
Date: 20151126

ACTIVE INGREDIENTS: IODINE 0.5 g/10 mL; POTASSIUM IODIDE 0.2 g/10 mL
INACTIVE INGREDIENTS: ETHANOL, 2-(BIS(2-METHYLPROPYL)PHENOXY)- 10 mL/10 mL; WATER 10 mL/10 mL

Drug facts

Active ingredients

Iodine - 0.5 g, Potassium Iodide - 0.2 g

Purpose

Bactericidial - antiseptic

Uses

For inflammatory and infectious diseases of skin, cuts, minor injuries, wounds, myositis, neuraldia; for disinfection of the operational field.

Warnings

For external use only.

Avoid contact with eyes. If contact occurs, rinse eyes throughly with water.

Stop use and ask a doctor if condition worsens or does not improve after regular use of this product as directed.

Keep out of reach of children. If swallowed, seek medical attention or contact a Poison Control center immediately.

Directions

Apply to affected areas as needed or as directed by physician.

Other information

Keep in a dark place at temperature below 25oC.

Inactive ingredients

Ethanol, Purified Water